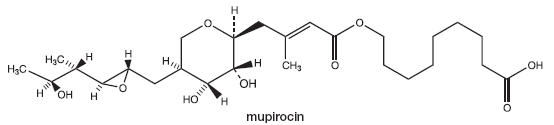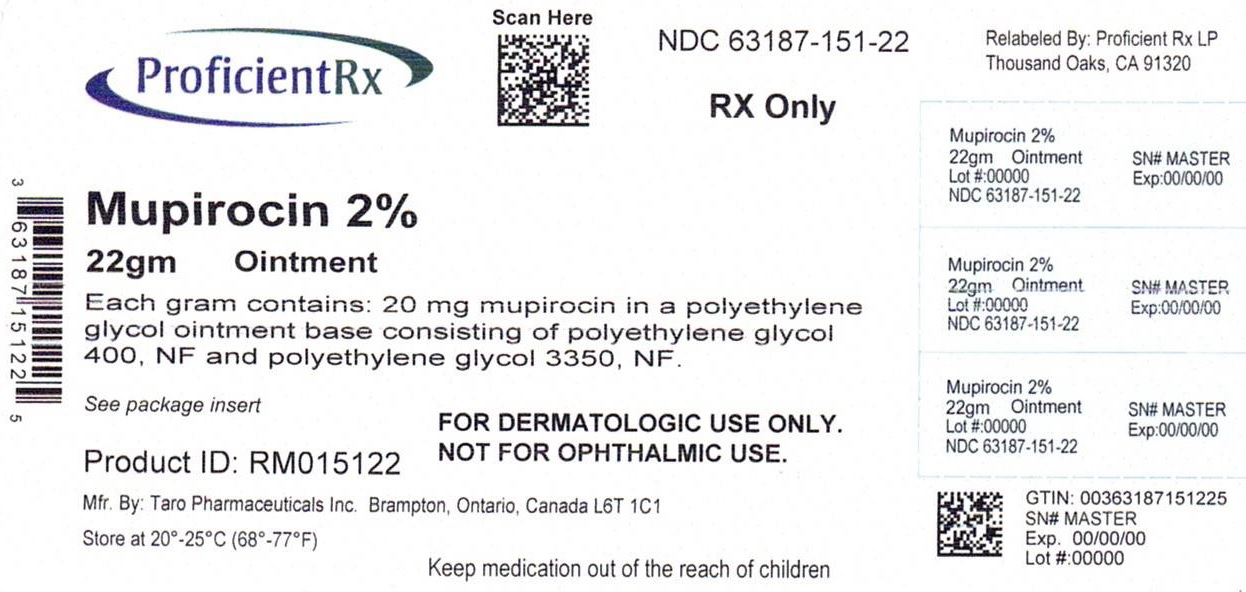 DRUG LABEL: Mupirocin
NDC: 63187-151 | Form: OINTMENT
Manufacturer: Proficient Rx LP
Category: prescription | Type: HUMAN PRESCRIPTION DRUG LABEL
Date: 20230101

ACTIVE INGREDIENTS: Mupirocin 20 mg/1 g
INACTIVE INGREDIENTS: polyethylene glycol 400; polyethylene glycol 3350

Mupirocin
Ointment USP, 2%

Rx only
For Dermatologic Use

DESCRIPTION

Each gram of Mupirocin Ointment USP, 2% contains 20 mg mupirocin in a bland water miscible ointment base (polyethylene glycol ointment, NF) consisting of polyethylene glycol 400 NF and polyethylene glycol 3350 NF. Mupirocin is a naturally occurring antibiotic. The chemical name is (E)-(2S,3R,4R,5S)-5-[(2S,3S,4S,5S)-2,3-Epoxy-5-hydroxy-4-methylhexyl]tetrahydro-3,4-dihydroxy-β-methyl-2H-pyran-2-crotonic acid, ester with 9-hydroxynonanoic acid. The molecular formula of mupirocin is C26H44O9, and the molecular weight is 500.63. The chemical structure is:

CLINICAL PHARMACOLOGY

Application of ^14C-labeled mupirocin ointment to the lower arm of normal male subjects followed by occlusion for 24 hours showed no measurable systemic absorption (<1.1 nanogram mupirocin per milliliter of whole blood). Measurable radioactivity was present in the stratum corneum of these subjects 72 hours after application.

Following intravenous or oral adminstration, mupirocin is rapidly metabolized. The principal metabolite, monic acid, is eliminated by renal excretion, and demonstrates no antibacterial activity. In a study conducted in seven healthy adult male subjects, the elimination half-life after intravenous administration of mupirocin was 20 to 40 minutes for mupirocin and 30 to 80 minutes for monic acid. The pharmacokinetics of mupirocin has not been studied in individuals with renal insufficiency.

MICROBIOLOGY

Microbiology: Mupirocin is an antibacterial agent produced by fermentation using the organism Pseudomonas fluorescens. It is active against a wide range of gram-positive bacteria including methicillin-resistant Staphylococcus aureus (MRSA). It is also active against certain gram-negative bacteria. Mupirocin inhibits bacterial protein synthesis by reversibly and specifically binding to bacterial isoleucyl transfer-RNA synthetase. Due to this unique mode of action, mupirocin demonstrates no in vitro cross-resistance with other classes of antimicrobial agents.

Resistance occurs rarely. However, when mupirocin resistance does occur, it appears to result from the production of a modified isoleucyl-tRNA synthetase. High-level plasmid-mediated resistance (MIC >1024 mcg/mL) has been reported in some strains of S. aureus and coagulase-negative staphylococci.

Mupirocin is bactericidal at concentrations achieved by topical administration. However, the minimum bactericidal concentration (MBC) against relevant pathogens is generally 8-fold to 30-fold higher than the minimum inhibitory concentration (MIC). In addition, mupirocin is highly protein bound (>97%), and the effect of wound secretions on the MICs of mupirocin has not been determined.

Mupirocin has been shown to be active against most strains of S. aureus and Streptococcus pyogenes, both in vitro and in clinical trials (see INDICATIONS AND USAGE). The following in vitro data are available, BUT THEIR CLINICAL SIGNIFICANCE IS UNKNOWN. Mupirocin is active against most strains of Staphylococcus epidermidis and Staphylococcus saprophyticus.

INDICATIONS AND USAGE

Mupirocin Ointment USP, 2% is indicated for the topical treatment of impetigo due to: S. aureus and S. pyogenes.

CONTRAINDICATIONS

This drug is contraindicated in patients with known hypersensitivity to any of the constituents of the product.

WARNINGS

Avoid contact with the eyes. In case of accidental contact, rinse well with water.

In the event of sensitization or severe local irritation from mupirocin ointment, usage should be discontinued.

Clostridium difficile-associated diarrhea (CDAD) has been reported with use of nearly all antibacterial agents, including mupirocin, and may range in severity from mild diarrhea to fatal colitis. Treatment with antibacterial agents alters the normal flora of the colon leading to overgrowth of C. difficile.

C. difficile produces toxins A and B which contribute to the development of CDAD. Hypertoxin producing isolates of C. difficile cause increased morbidity and mortality, as these infections can be refractory to antimicrobial therapy and may require colectomy. CDAD must be considered in all patients who present with diarrhea following antibacterial drug use. Careful medical history is necessary since CDAD has been reported to occur over two months after the administration of antibacterial agents.

If CDAD is suspected or confirmed, ongoing antibacterial drug use not directed against C. difficile may need to be discontinued. Appropriate fluid and electrolyte management, protein supplementation, antibacterial treatment of C. difficile, and surgical evaluation should be instituted as clinically indicated.

PRECAUTIONS

As with other antibacterial products, prolonged use may result in overgrowth of nonsusceptible organisms, including fungi.

Mupirocin ointment is not formulated for use on mucosal surfaces. Intranasal use has been associated with isolated reports of stinging and drying.

Polyethylene glycol can be absorbed from open wounds and damaged skin and is excreted by the kidneys. In common with other polyethylene glycol-based ointments, mupirocin ointment should not be used in conditions where absorption of large quantities of polyethylene glycol is possible, especially if there is evidence of moderate or severe renal impairment.

Mupirocin ointment should not be used with intravenous cannulae or at central intravenous sites because of the potential to promote fungal infections and antimicrobial resistance.

PATIENT COUNSELING INFORMATION

Information for Patients: Use this medication only as directed by the healthcare provider. It is for external use only. Avoid contact with the eyes. If mupirocin ointment gets in or near the eyes, rinse thoroughly with water. The medication should be stopped and the healthcare provider contacted if irritation, severe itching, or rash occurs.

If impetigo has not improved in 3 to 5 days, contact the healthcare provider.

DRUG INTERACTIONS

Drug Interactions: The effect of the concurrent application of mupirocin ointment and other drug products has not been studied.

CARCINOGENESIS AND MUTAGENESIS AND IMPAIRMENT OF FERTILITY

Carcinogenesis, Mutagenesis, Impairment of Fertility: Long-term studies in animals to evaluate carcinogenic potential of mupirocin have not been conducted.

Results of the following studies performed with mupirocin calcium or mupirocin sodium in vitro and in vivo did not indicate a potential for genotoxicity: Rat primary hepatocyte unscheduled DNA synthesis, sediment analysis for DNA strand breaks, Salmonella reversion test (Ames), Escherichia coli mutation assay, metaphase analysis of human lymphocytes, mouse lymphoma assay, and bone marrow micronuclei assay in mice.

Reproduction studies were performed in male and female rats with mupirocin administered subcutaneously at doses up to 14 times a human topical dose (approximately 60 mg mupirocin per day) on a mg/m^2 basis and revealed no evidence of impaired fertility and reproductive performance from mupirocin.

PREGNANCY

TERATOGENIC EFFECTS

Pregnancy: Teratogenic Effects: Pregnancy Category B: Reproduction studies have been performed in rats and rabbits with mupirocin administered subcutaneously at doses up to 22 and 43 times, respectively, the human topical dose (approximately 60 mg mupirocin per day) on a mg/m^2 basis and revealed no evidence of harm to the fetus due to mupirocin. There are, however, no adequate and well-controlled studies in pregnant women. Because animal studies are not always predictive of human response, this drug should be used during pregnancy only if clearly needed.

NURSING MOTHERS

Nursing Mothers: It is not known whether this drug is excreted in human milk. Because many drugs are excreted in human milk, caution should be exercised when mupirocin ointment is administered to a nursing woman.

PEDIATRIC USE

Pediatric Use: The safety and effectiveness of mupirocin ointment have been established in the age range of 2 months to 16 years. Use of mupirocin ointment in these age groups is supported by evidence from adequate and well-controlled trials of mupirocin ointment in impetigo in pediatric subjects studied as a part of the pivotal clinical trials (see CLINICAL STUDIES).

ADVERSE REACTIONS

The following local adverse reactions have been reported in connection with the use of mupirocin ointment: burning, stinging, or pain in 1.5% of subjects; itching in 1% of subjects; rash, nausea, erythema, dry skin, tenderness, swelling, contact dermatitis, and increased exudate in less than 1% of subjects.

Systemic allergic reactions, including anaphylaxis, urticaria, angioedema and generalized rash have been reported in patients treated with mupirocin formulations.

DOSAGE AND ADMINISTRATION

A small amount of mupirocin ointment should be applied to the affected area 3 times daily. The area treated may be covered with a gauze dressing if desired. Patients not showing a clinical response within 3 to 5 days should be re-evaluated.

CLINICAL STUDIES

The efficacy of topical mupirocin ointment in impetigo was tested in 2 trials. In the first, subjects with impetigo were randomized to receive either mupirocin ointment or vehicle placebo 3 times daily for 8 to 12 days. Clinical efficacy rates at end of therapy in the evaluable populations (adults and pediatric subjects included) were 71% for mupirocin ointment (n=49) and 35% for vehicle placebo (n=51). Pathogen eradication rates in the evaluable populations were 94% for mupirocin ointment and 62% for vehicle placebo. There were no side effects reported in the group receiving mupirocin ointment.

In the second trial, subjects with impetigo were randomized to receive either mupirocin ointment 3 times daily or 30 to 40 mg/kg oral erythromycin ethylsuccinate per day (this was an unblinded trial) for 8 days. There was a follow-up visit 1 week after treatment ended. Clinical efficacy rates at the follow-up visit in the evaluable populations (adults and pediatric subjects included) were 93% for mupirocin ointment (n=29) and 78.5% for erythromycin (n=28). Pathogen eradication rates in the evaluable populations were 100% for both test groups. There were no side effects reported in the group receiving mupirocin ointment.

Pediatrics: There were 91 pediatric subjects aged 2 months to 15 years in the first trial described above. Clinical efficacy rates at end of therapy in the evaluable populations were 78% for mupirocin ointment (n=42) and 36% for vehicle placebo (n=49). In the second trial described above, all subjects were pediatric except 2 adults in the group receiving mupirocin ointment. The age range of the pediatric subjects was 7 months to 13 years. The clinical efficacy rate for mupirocin ointment (n=27) was 96%, and for erythromycin it was unchanged (78.5%).

HOW SUPPLIED

Mupirocin Ointment USP, 2% is supplied in 22 g (NDC 63187-151-22) tubes.

STORAGE AND HANDLING

Store at 20°-25°C (68°-77°F) [see USP Controlled Room Temperature].

Mfd. by: Taro Pharmaceuticals Inc., Brampton, Ontario, Canada L6T 1C1
Dist. by: Taro Pharmaceuticals U.S.A., Inc., Hawthorne, NY 10532
Revised: June 2014

PK-4402-1 358

Relabeled by:
Proficient Rx LP
Thousand Oaks, CA 91320